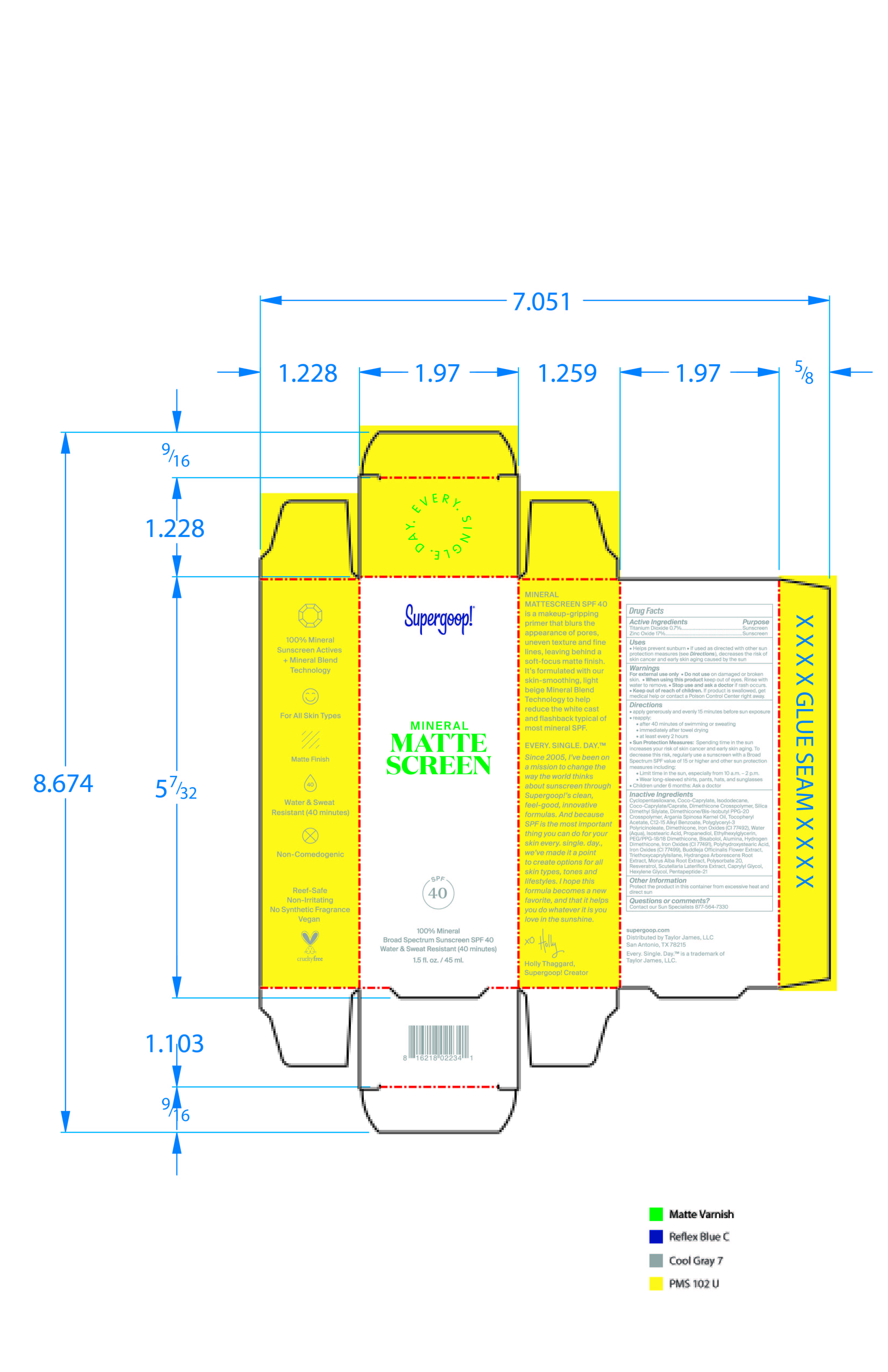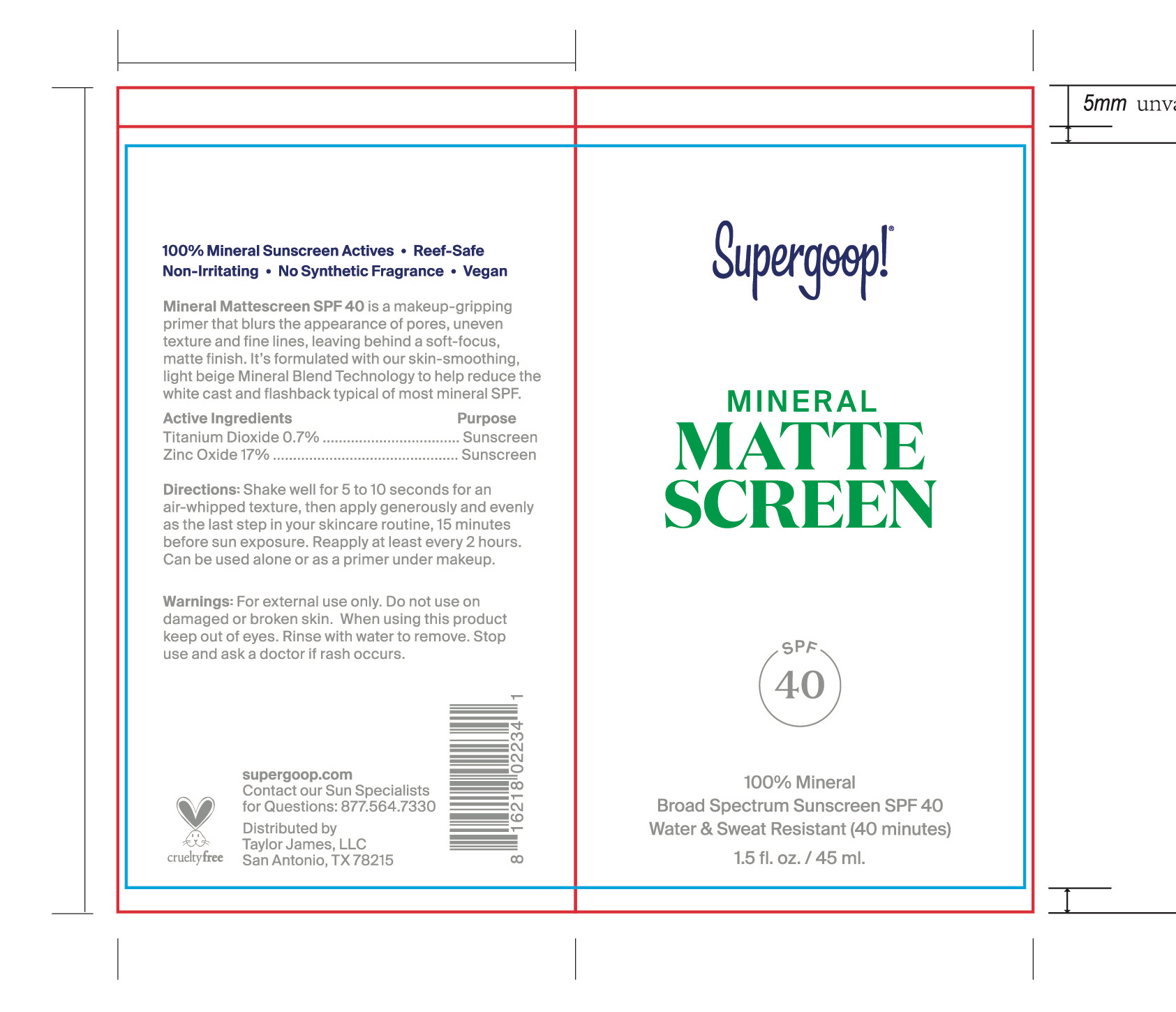 DRUG LABEL: Mineral Mattescreen Broad Spectrum SPF 40
NDC: 75936-280 | Form: LOTION
Manufacturer: Taylor James
Category: otc | Type: HUMAN OTC DRUG LABEL
Date: 20210426

ACTIVE INGREDIENTS: TITANIUM DIOXIDE 0.7 g/100 mL; ZINC OXIDE 17 g/100 mL
INACTIVE INGREDIENTS: LEVOMENOL; HYDROGEN DIMETHICONE (13 CST); POLYHYDROXYSTEARIC ACID (2300 MW); FERROSOFERRIC OXIDE; TRIETHOXYCAPRYLYLSILANE; PHENOXYETHANOL; POTASSIUM SORBATE; HYDRANGEA ARBORESCENS ROOT; MORUS ALBA ROOT; POLYSORBATE 20; CAPRYLYL GLYCOL; HEXYLENE GLYCOL; FERRIC OXIDE YELLOW; PEG/PPG-18/18 DIMETHICONE; FERRIC OXIDE RED; TOCOPHEROL; RESVERATROL; .ALPHA.-TOCOPHEROL ACETATE; ALKYL (C12-15) BENZOATE; CYCLOMETHICONE 6; DIMETHICONE/BIS-ISOBUTYL PPG-20 CROSSPOLYMER; DIMETHICONE; BUDDLEJA OFFICINALIS FLOWER; SCUTELLARIA LATERIFLORA; ISOSTEARIC ACID; PROPANEDIOL; ETHYLHEXYLGLYCERIN; CYCLOMETHICONE 5; COCO-CAPRYLATE; COCO-CAPRYLATE/CAPRATE; DIMETHICONE/VINYL DIMETHICONE CROSSPOLYMER (SOFT PARTICLE); SILICA DIMETHYL SILYLATE; ARGAN OIL; WATER; ALUMINUM OXIDE

Mineral Mattescreen SPF 40

Active ingredients Purpose

Zinc oxide 17% Sunscreen

Titanium dioxide 0.7% Sunscreen

Uses

- Helps prevent Sunburn
- If used as directed with other sun protection (see Directions), decreases the risk of skin cancer and early skin aging caused by the sun.

Keep out of reach of children. If product is swallowed, get medical help or contact a Poison Control Center right away.

Warnings

For external use only

Do not use on damaged or broken skin

When using this product keep out of eyes. Rinse with water to remove.

Stop use and ask a doctor if rash occurs.

Directions

- apply generously and evenly 15 minutes before sun exposure
- reapply:
- after 40 minutes of swimming or sweating
- immediately after towel drying
- at least 2 hours
- Sun Protection Measures Spending time in the sun increases your risk of skin cancer and early skin aging. To decrease this risk of skin cancer and early skin aging, regularly use a sunscreen with a Broad Spectrum SPF value of 15 or higher and other sun protection measures including:
- Limit time in the sun, especially from 10 a.m. -2p.m.
- Wear Long-sleeved shirts, pants, hats, and sunglasses
- Children under 6 months: Ask a doctor

Inactive ingredients

Cyclopentasiloxane, Coco-Caprylate, Isododecane, Coco-Caprylate/Caprate, Dimethicone Crosspolymer, Silica Dimethyl Silylate, Dimethicone/Bis-Isobutyl PPG-20 Crosspolymer, Argania Spinosa Kernel Oil, Cyclohexasiloxane, Tocopheryl Acetate, C12-15 Alkyl Benzoate, Polyglyceryl-3 Polyricinoleate, Dimethicone, Iron Oxides (CI 77492), Water (Aqua), Isostearic Acid, Cyclotetrasiloxane, Propanediol, Ethylhexylglycerin, PEG/PPG-18/18 Dimethicone, Bisabolol, Alumina, Hydrogen Dimethicone, Iron Oxides (CI 77491),

Polyhydroxystearic Acid, Iron Oxides (CI 77499), Buddleja Officinalis Flower Extract, Triethoxycaprylylsilance, Tocopherol, Phenoxyethanol, Potassium Sorbate, Hydrangea Aborescens Root Extract, Morus Alba Root Extract, Polysorbate 20, Resveratrol, Scutellaria Lateriflora Extract, Caprylyl Glycol, Hexylene Glycol, Pentapeptide-21

PACKAGE LABEL

Supergoop!

Mineral

MATTE

SCREEEN

100% mineral

Broad Spectrum SPF 40

Water & Sweat Resistant (40 minutes)

1.5 fl. oz/ 45 mL